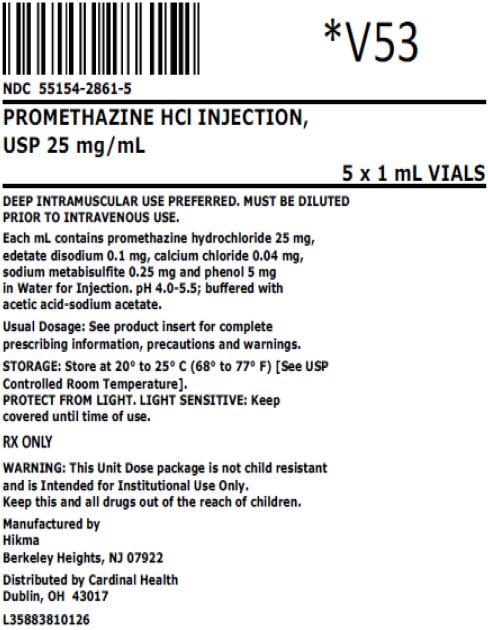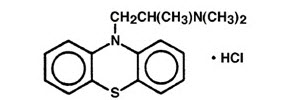 DRUG LABEL: Promethazine Hydrochloride
NDC: 55154-2861 | Form: INJECTION
Manufacturer: Cardinal Health 107, LLC
Category: prescription | Type: HUMAN PRESCRIPTION DRUG LABEL
Date: 20260115

ACTIVE INGREDIENTS: PROMETHAZINE HYDROCHLORIDE 25 mg/1 mL
INACTIVE INGREDIENTS: EDETATE DISODIUM 0.1 mg/1 mL; CALCIUM CHLORIDE 0.04 mg/1 mL; SODIUM METABISULFITE 0.25 mg/1 mL; PHENOL 5 mg/1 mL; WATER; ACETIC ACID; SODIUM ACETATE

Promethazine Hydrochloride Injection, USP

Rx only

WARNING: RESPIRATORY DEPRESSION IN PEDIATRICS AND SEVERE TISSUE INJURY, INCLUDING GANGRENE

Respiratory Depression – Pediatrics

- Promethazine hydrochloride injection should not be used in pediatric patients less than 2 years of age because of the potential for fatal respiratory depression. Postmarketing cases of respiratory depression, including fatalities, have been reported with use of promethazine in pediatric patients less than 2 years of age. Caution should be exercised when administering promethazine hydrochloride injection to pediatric patients 2 years of age and older (See Warning – Respiratory Depression)

Severe Tissue Injury, Including Gangrene

- Severe chemical irritation and damage to tissues regardless of the route of parenteral administration has been reported in patients treated with promethazine hydrochloride injection including gangrene, tissue necrosis, and thrombophlebitis; and in some cases, surgical intervention including fasciotomy, skin graft, and/or amputation have been required (see WARNINGS – Severe Tissue Injury, Including Gangrene.).
- The use of promethazine hydrochloride injection by the following routes of administration is CONTRAINDICATED:
- Intravenous injection at concentrations greater than 1 mg/mL
- Intra-arterial injection
- Subcutaneous injection (see CONTRAINDICATIONS).
- The preferred route of administration is by deep intramuscular administration.
- Promethazine hydrochloride injection may be administered intravenously after dilution through an intravenous catheter inserted in a large vein. Preferably through a central venous catheter (see DOSAGE AND ADMINISTRATION).
- If pain occurs at the injection site during intravenous infusion, immediately discontinue the infusion and evaluate for possible arterial injection or perivascular extravasation, and initiate appropriate medical management.

DESCRIPTION

Promethazine hydrochloride injection, USP is a sterile, pyrogen-free solution for deep intramuscular or intravenous administration. Promethazine hydrochloride (10H-Phenothiazine-10-ethanamine,N,N,α-trimethyl-, monohydrochloride, (±)-) is a racemic compound and has the following structural formula:

C17H21ClN2S MW 320.88

Each mL contains promethazine hydrochloride, either 25 mg or 50 mg, edetate disodium 0.1 mg, calcium chloride 0.04 mg, sodium metabisulfite 0.25 mg and phenol 5 mg in Water for Injection. pH 4.0 to 5.5; buffered with acetic acid-sodium acetate.
Promethazine hydrochloride injection is a clear, colorless solution. The product is light sensitive. It should be inspected before use and discarded if either color or particulate is observed.

CLINICAL PHARMACOLOGY

Promethazine hydrochloride is a phenothiazine derivative which possesses antihistaminic, sedative, antimotion-sickness, antiemetic, and anticholinergic effects. Promethazine is a competitive H1 receptor antagonist, but does not block the release of histamine. Structural differences from the neuroleptic phenothiazines result in its relative lack (1/10 that of chlorpromazine) of dopamine antagonist properties. Clinical effects are generally apparent within 5 minutes of an intravenous injection and within 20 minutes of an intramuscular injection. Duration of action is four to six hours, although effects may persist up to 12 hours. Promethazine hydrochloride is metabolized in the liver, with the sulfoxides of promethazine and N-desmethylpromethazine being the predominant metabolites appearing in the urine. Following intravenous administration in healthy volunteers, the plasma half-life for promethazine has been reported to range from 9 to 16 hours. The mean plasma half-life for promethazine after intramuscular administration in healthy volunteers has
been reported to be 9.8 ± 3.4 hours.

INDICATIONS AND USAGE

Promethazine hydrochloride injection is indicated for the following conditions:

- Amelioration of allergic reactions to blood or plasma.
- In anaphylaxis as an adjunct to epinephrine and other standard measures after the acute symptoms have been controlled.
- For other uncomplicated allergic conditions of the immediate type when oral therapy is impossible or contraindicated.
- For sedation and relief of apprehension and to produce light sleep from which the patient can be easily aroused.
- Active treatment of motion sickness.
- Prevention and control of nausea and vomiting associated with certain types of anesthesia and surgery.
- As an adjunct to analgesics for the control of postoperative pain.
- Preoperative, postoperative, and obstetric (during labor) sedation.
- Intravenously in special surgical situations, such as repeated bronchoscopy, ophthalmic surgery, and poor-risk patients, with reduced amounts of meperidine or other narcotic analgesic as an adjunct to anesthesia and analgesia.

CONTRAINDICATIONS

The use of promethazine hydrochloride injection is contraindicated:

- In pediatric patients less than 2 years of age due to the risk of respiratory depression (see WARNINGS – Respiratory Depression).
- For use as an intravenous injection at concentrations greater than 1 mg/mL due to the risk of perivascular extravasation, unintentional intra-arterial injection, and intraneuronal or perineuronal infiltration (see WARNINGS - Severe Tissue Injury, Including Gangrene and DOSAGE AND ADMINISTRATION).
- For use as an intra-arterial injection due to the likelihood of severe arteriospasm and the possibility of resultant gangrene (see WARNINGS - Severe Tissue Injury, Including Gangrene).
- For use as a subcutaneous injection because chemical irritation and necrotic lesions have been reported (see WARNINGS - Severe Tissue Injury, Including Gangrene).
- In patients in a comatose state.
- In patients who have demonstrated an idiosyncratic reaction or hypersensitivity to promethazine hydrochloride or other phenothiazines.

WARNINGS

Respiratory Depression

Pediatrics

Promethazine hydrochloride injection should not be used in pediatric patients less than 2 years of age because of the potential for fatal respiratory depression. Postmarketing cases of respiratory depression, including fatalities, have been reported with use of promethazine in pediatric patients less than 2 years of age. A wide range of weight-based doses of promethazine hydrochloride injection have resulted in respiratory depression in these patients.

Caution should be exercised when administering promethazine hydrochloride injection to pediatric patients 2 years of age and older. It is recommended that the lowest effective dose of promethazine hydrochloride injection be used in pediatric patients 2 years of age and older. Avoid concomitant administration of other drugs with respiratory depressant effects because of an association with respiratory depression, and sometimes death, in pediatric patients.

Other

Because of the risk of potentially fatal respiratory depression, use of promethazine hydrochloride injection in patients with compromised respiratory function or patients at risk for respiratory failure (e.g. COPD, sleep apnea) should be avoided.

Severe Tissue Injury, Including Gangrene

- Promethazine hydrochloride injection has been reported to cause severe chemical irritation and damage to tissues, including gangrene, regardless of the route of parenteral administration. Intra-arterial and subcutaneous administration have resulted in more significant complications. The use of promethazine hydrochloride injection by intravenous injection at concentrations greater than 1 mg/mL, intra- arterial injection, or subcutaneous injection is contraindicated (see CONTRAINDICATIONS).
- Irritation and damage can result from perivascular extravasation, intra- arterial injection, and intraneuronal or perineuronal infiltration. Inadvertent intra-arterial injection can cause severe arteriospasm. Other reported adverse reactions included burning, pain, erythema, swelling, sensory loss, palsies, paralysis, severe spasm of distal vessels, thrombophlebitis, venous thrombosis, phlebitis, abscesses, tissue necrosis, and gangrene. In some cases, surgical intervention, including fasciotomy, skin graft, and/or amputation have been required.
- The preferred route of administration of promethazine hydrochloride injection is by deep intramuscular administration.
- Promethazine hydrochloride injection may be administered intravenously after dilution through an intravenous catheter inserted in a large vein. Preferably through a central venous catheter (see DOSAGE AND ADMINISTRATION).
- If pain occurs at the injection site during intravenous infusion, immediately discontinue the infusion, evaluate for possible arterial injection or perivascular extravasation, and initiate appropriate medical management.

CNS Depression

Promethazine hydrochloride injection may impair the mental and/or physical abilities required for the performance of potentially hazardous tasks, such as driving a vehicle or operating machinery.

The impairment may be amplified by concomitant use of other central-nervous-system depressants such as alcohol, sedative/hypnotics (including barbiturates), general anesthetics, narcotics, narcotic analgesics, tricyclic antidepressants, and tranquilizers; therefore such agents should either be eliminated or given in reduced dosage in the presence of promethazine hydrochloride (see PRECAUTIONS - Information for Patients and Drug Interactions).

Lower Seizure Threshold

Promethazine hydrochloride injection may lower seizure threshold and should be used with caution in persons with seizure disorders or in persons who are using concomitant medications, such as narcotics or local anesthetics, which may also affect seizure threshold.

Bone-Marrow Depression

Promethazine hydrochloride injection should be used with caution in patients with bone-marrow depression. Leukopenia and agranulocytosis have been reported, usually when promethazine hydrochloride has been used in association with other known marrow-toxic agents.

Neuroleptic Malignant Syndrome

A potentially fatal symptom complex sometimes referred to as Neuroleptic Malignant Syndrome (NMS) has been reported in association with promethazine hydrochloride alone or in combination with antipsychotic drugs. Clinical manifestations of NMS are hyperpyrexia, muscle rigidity, altered mental status and evidence of autonomic instability (irregular pulse or blood pressure, tachycardia, diaphoresis and cardiac dysrhythmias).

The diagnostic evaluation of patients with this syndrome is complicated. In arriving at a diagnosis, it is important to identify cases where the clinical presentation includes both serious medical illness (e.g., pneumonia, systemic infection, etc.) and untreated or inadequately treated extrapyramidal signs and symptoms (EPS). Other important considerations in the differential diagnosis include central anticholinergic toxicity, heat stroke, drug fever and primary central nervous system (CNS) pathology.

The management of NMS should include 1) immediate discontinuation of promethazine hydrochloride, antipsychotic drugs, if any, and other drugs not essential to concurrent therapy, 2) intensive symptomatic treatment and medical monitoring, and 3) treatment of any concomitant serious medical problems for which specific treatments are available. There is no general agreement about specific pharmacological treatment regimens for uncomplicated NMS.

Since recurrences of NMS have been reported with phenothiazines, the reintroduction of promethazine hydrochloride should be carefully considered.

Sulfite Sensitivity

Promethazine hydrochloride injection contains sodium metabisulfite, a sulfite that may cause allergic-type reactions, including anaphylactic symptoms and life-threatening or less severe asthma episodes, in certain susceptible people. The overall prevalence of sulfite sensitivity in the general population is unknown and probably low. Sulfite sensitivity is seen more frequently in asthmatic than in nonasthmatic people.

Visual Inspection

This product is light sensitive and should be inspected before use and discarded if either color or particulate is observed.

Cholestatic Jaundice

Administration of promethazine has been associated with reported cholestatic jaundice.

PRECAUTIONS

General

Drugs having anticholinergic properties should be used with caution in patients with narrow-angle glaucoma, prostatic hypertrophy, stenosing peptic ulcer, pyloroduodenal obstruction, and bladder-neck obstruction.
Promethazine hydrochloride injection should be used cautiously in persons with cardiovascular disease or impairment of liver function.

Information for Patients

Patients should be advised of the risk of respiratory depression, including potentially fatal respiratory depression in children less than 2 years of age (see WARNINGS - Respiratory Depression).

Patients should be advised of the risk of severe tissue injury, including gangrene (see WARNINGS - Severe Tissue Injury, Including Gangrene). Patients should be advised to immediately report persistent or worsening pain or burning at the injection site.

Promethazine hydrochloride injection may cause marked drowsiness or impair the mental or physical abilities required for the performance of potentially hazardous tasks, such as driving a vehicle or operating machinery. Pediatric patients should be supervised to avoid potential harm in bike riding or in other hazardous activities. The concomitant use of alcohol, sedative/hypnotics (including barbiturates), general anesthetics, narcotics, narcotic analgesics, tricyclic antidepressants, and tranquilizers may enhance impairment (see WARNINGS - CNS Depression and PRECAUTIONS - Drug Interactions).

Patients should be advised to report any involuntary muscle movements (see ADVERSE REACTIONS - Paradoxical Reactions).

Patients should be advised to avoid prolonged exposure to the sun (see ADVERSE REACTIONS - Dermatologic).

Drug Interactions

CNS Depressants

Promethazine hydrochloride injection may increase, prolong, or intensify the sedative action of central-nervous-system depressants, such as alcohol, sedative/hypnotics (including barbiturates), general anesthetics, narcotics, narcotic analgesics, tricyclic antidepressants, and tranquilizers; therefore, such agents should be avoided or administered in reduced dosage to patients receiving promethazine hydrochloride. When given concomitantly with promethazine hydrochloride injection, the dose of barbiturates should be reduced by at least one-half, and the dose of narcotics should be reduced by one-quarter to one-half. Dosage must be individualized. Excessive amounts of promethazine hydrochloride injection relative to a narcotic may lead to restlessness and motor hyperactivity in the patient with pain; these symptoms usually disappear with adequate control of the pain.

Epinephrine

Because of the potential for promethazine hydrochloride to reverse epinephrine’s vasopressor effect, epinephrine should NOT be used to treat hypotension associated with promethazine hydrochloride injection overdose.

Anticholinergics

Concomitant use of other agents with anticholinergic properties should be undertaken with caution.

Monoamine Oxidase (MAO) Inhibitors

Drug interactions, including an increased incidence of extrapyramidal effects, have been reported when some MAO Inhibitors and phenothiazines are used concomitantly. This possibility should be considered with promethazine hydrochloride injection.

Drug/Laboratory Test Interactions

The following laboratory tests may be affected in patients who are receiving therapy with promethazine hydrochloride injection:

Pregnancy Tests

Diagnostic pregnancy tests based on immunological reactions between HCG and anti-HCG may result in false-negative or false-positive interpretations.

Glucose Tolerance Test

An increase in blood glucose has been reported in patients receiving promethazine hydrochloride.

Carcinogenesis, Mutagenesis and Impairment of Fertility

Long-term animal studies have not been performed to assess the carcinogenic potential of promethazine hydrochloride injection, nor are there other animal or human data concerning carcinogenicity, mutagenicity, or impairment of fertility.
Promethazine hydrochloride injection was nonmutagenic in the Salmonella test system of Ames.

Pregnancy

Teratogenic Effects—Pregnancy Category C

Teratogenic effects have not been demonstrated in rat-feeding studies at doses of 6.25 and 12.5 mg/kg (approximately 2.1 and 4.2 times the maximum recommended human daily dose) of promethazine hydrochloride injection. Daily doses of 25 mg/kg intraperitoneally have been found to produce fetal mortality in rats.

There are no adequate and well-controlled studies of promethazine hydrochloride injection in pregnant women. Because animal reproduction studies are not always predictive of human response, promethazine hydrochloride injection should be used during pregnancy only if the potential benefit justifies the potential risk to the fetus.

Adequate studies to determine the action of the drug on parturition, lactation and development of the animal neonate have not been conducted.

Nonteratogenic Effects

Promethazine hydrochloride injection administered to a pregnant woman within two weeks of delivery may inhibit platelet aggregation in the newborn.

Labor and Delivery

Promethazine hydrochloride injection may be used alone or as an adjunct to narcotic analgesics during labor (see DOSAGE AND ADMINISTRATION). Limited data suggest that use of promethazine hydrochloride injection during labor and delivery does not have an appreciable effect on the duration of labor or delivery and does not increase the risk of need for intervention in the newborn. The effect on later growth and development of the newborn is unknown. (See also Pregnancy - Nonteratogenic Effects.)

Nursing Mothers

It is not known whether promethazine hydrochloride injection is excreted in human milk. Because many drugs are excreted in human milk, and because of the potential for serious adverse reactions in nursing infants from promethazine hydrochloride injection, a decision should be made whether to discontinue nursing or to discontinue the drug, taking into
account the importance of the drug to the mother.

Pediatric Use

Promethazine hydrochloride injection is contraindicated for use in pediatric patients less than 2 years of age, because of the potential for fatal respiratory depression. Promethazine hydrochloride injection should be used with caution in pediatric patients 2 years of age and older (see WARNINGS - Respiratory Depression).

Antiemetics are not recommended for treatment of uncomplicated vomiting in pediatric patients, and their use should be limited to prolonged vomiting of known etiology. The extrapyramidal symptoms which can occur secondary to promethazine hydrochloride injection administration may be confused with the CNS signs of undiagnosed primary disease,
e.g. encephalopathy or Reye’s syndrome. The use of promethazine hydrochloride injection should be avoided in pediatric patients whose signs and symptoms may suggest Reye’s syndrome or other hepatic diseases.

Excessively large dosages of antihistamines, including promethazine hydrochloride injection, in pediatric patients may cause sudden death (see OVERDOSAGE). Hallucinations and convulsions have occurred with therapeutic doses and overdoses of promethazine hydrochloride injection in pediatric patients. In pediatric patients who are acutely ill associated with dehydration, there is an increased susceptibility to dystonias with the use of promethazine hydrochloride injection.

Geriatric Use (patients approximately 60 years or older)

Since therapeutic requirements for sedative drugs tend to be less in geriatric patients, the dosage should be reduced for these patients.

ADVERSE REACTIONS

Respiratory Depression

Promethazine hydrochloride injection is contraindicated in pediatric patients less than 2 years of age, because of the potential for fatal respiratory depression. Promethazine hydrochloride injection should be used with caution in pediatric patients 2 years of age and older (see WARNINGS - Respiratory Depression).

Severe Tissue Injury, Including Gangrene

Promethazine hydrochloride injection has been reported to cause severe chemical irritation and damage to tissues, including gangrene, regardless of the route of parenteral administration. Intra-arterial and subcutaneous injection have resulted in more significant complications (see CONTRAINDICATIONS). Reported adverse reactions included burning, pain, erythema, swelling, sensory loss, palsies, paralysis, severe spasm of distal vessels, thrombophlebitis, venous thrombosis, phlebitis, abscesses, tissue necrosis, and gangrene (see WARNINGS - Severe Tissue Injury, Including Gangrene).

Central Nervous System

Drowsiness is the most prominent CNS effect of this drug. Sedation, somnolence, blurred vision, dizziness, confusion, disorientation, and extrapyramidal symptoms such as oculogyric crisis, torticollis, and tongue protrusion; lassitude, tinnitus, incoordination, fatigue, euphoria, nervousness, diplopia, insomnia, tremors, convulsive seizures, excitation, catatonic-like states, hysteria. Hallucinations have also been reported.

Cardiovascular

Increased or decreased blood pressure, tachycardia, bradycardia, faintness.

Dermatologic

Dermatitis, photosensitivity, urticaria.

Hematologic

Leukopenia, thrombocytopenia, thrombocytopenic purpura, agranulocytosis.

Gastrointestinal

Dry mouth, nausea, vomiting, jaundice.

Respiratory

Asthma, nasal stuffiness, respiratory depression (potentially fatal) and apnea (potentially fatal). (See WARNINGS - Respiratory Depression.)

Other

Angioneurotic edema. Neuroleptic Malignant Syndrome (potentially fatal) has also been reported. (See WARNINGS - Neuroleptic Malignant Syndrome.)

Paradoxical Reactions

Hyperexcitability and abnormal movements have been reported in patients following a single administration of promethazine hydrochloride injection. Consideration should be given to the discontinuation of promethazine hydrochloride injection and to the use of other drugs if these reactions occur. Respiratory depression, nightmares, delirium, and agitated behavior have also been reported in some of these patients.

OVERDOSAGE

Signs and symptoms of overdosage range from mild depression of the central nervous system and cardiovascular system to profound hypotension, respiratory depression, unconsciousness and sudden death. Other reported reactions include hyperreflexia, hypertonia, ataxia, athetosis, and extensor-plantar reflexes (Babinski reflex).
Stimulation may be evident, especially in pediatric patients and geriatric patients. Convulsions may rarely occur.

A paradoxical-type reaction has been reported in pediatric patients receiving single doses of 75 mg to 125 mg orally, characterized by hyperexcitability and nightmares.

Atropine-like signs and symptoms-dry mouth; fixed, dilated pupils; flushing; etc., as well as gastrointestinal symptoms, may occur.

Treatment

Treatment of overdosage is essentially symptomatic and supportive. Only in cases of extreme overdosage or individual sensitivity do vital signs, including respiration, pulse, blood pressure, temperature, and EKG, need to be monitored.
Attention should be given to the reestablishment of adequate respiratory exchange through provision of a patent airway and institution of assisted or controlled ventilation. Diazepam may be used to control convulsions. Acidosis and electrolyte losses should be corrected. Note that any depressant effects of promethazine hydrochloride injection are not reversed by naloxone.

Avoid analeptics, which may cause convulsions. The treatment of choice for resulting hypotension is administration of intravenous fluids, accompanied by repositioning if indicated. In the event that vasopressors are considered for the management of severe hypotension which does not respond to intravenous fluids and repositioning, the administration of norepinephrine or phenylephrine should be considered. EPINEPHRINE SHOULD NOT BE USED, since its use in a patient with partial adrenergic blockade may further lower the blood pressure. Extrapyramidal reactions may be treated with anticholinergic antiparkinson agents, diphenhydramine, or barbiturates. Oxygen may also be administered. Limited
experience with dialysis indicates that it is not helpful.

DOSAGE AND ADMINISTRATION

Important Administration Information for Adult and Pediatric Patients 2 Years of Age and Older

- The preferred route of administration of promethazine hydrochloride injection is by deep intramuscular administration (see WARNINGS - Severe Tissue Injury, Including Gangrene).
- Promethazine hydrochloride injection may be administered intravenously after dilution as recommended below (see Preparation and Administration). If pain occurs at the injection site during intravenous infusion, immediately discontinue the infusion, and evaluate for possible arterial injection or perivascular extravasation.

Allergic Conditions

The average adult dose is 25 mg. This dose may be repeated within two hours if necessary, but continued therapy, if indicated, should be via the oral route as soon as existing circumstances permit. After initiation of treatment, dosage should be adjusted to the smallest amount adequate to relieve symptoms. The average adult dose for amelioration of allergic reactions to blood or plasma is 25 mg.

Sedation

In hospitalized adult patients, nighttime sedation may be achieved by a dose of 25 to 50 mg of promethazine hydrochloride injection.

Nausea and Vomiting

For control of nausea and vomiting, the usual adult dose is 12.5 to 25 mg, not to be repeated more frequently than every four hours. When used for control of postoperative nausea and vomiting, the dosage of analgesics and barbiturates should be reduced accordingly (see PRECAUTIONS - Drug Interactions).

Antiemetics should not be used in vomiting of unknown etiology in children and adolescents (see PRECAUTIONS - Pediatric Use).

Preoperative and Postoperative Use

As an adjunct to preoperative or postoperative medication, 25 to 50 mg of promethazine hydrochloride injection in adults may be combined with appropriately reduced doses of analgesics and atropine-like drugs as desired.

Dosage of concomitant analgesic or hypnotic medication should be reduced accordingly (see PRECAUTIONS - Drug Interactions).

Promethazine hydrochloride is contraindicated for use in pediatric patients less than two years of age.

Obstetrics

Promethazine hydrochloride injection in doses of 50 mg will provide sedation and relieve apprehension in the early stages of labor. When labor is definitely established, 25 to 75 mg (average dose, 50 mg) promethazine hydrochloride injection may be given with an appropriately reduced dose of any desired narcotic (see PRECAUTIONS - Drug Interactions). If necessary, promethazine hydrochloride injection with a reduced dose of analgesic may be repeated once or twice at four-hour intervals in the course of a normal labor. A maximum total dose of 100 mg of promethazine hydrochloride injection may be administered during a 24-hour period to patients in labor.

Pediatric Patients

Promethazine hydrochloride injection is contraindicated for use in pediatric patients less than 2 years of age (see WARNINGS - Respiratory Depression). Caution should be exercised when administering promethazine hydrochloride to pediatric patients 2 years of age or older. It is recommended that the lowest effective dose of promethazine hydrochloride be used in pediatric patients 2 years of age and older and concomitant administration of other drugs with respiratory depressant effects be avoided (see WARNINGS - Respiratory Depression).

In pediatric patients 2 years of age and older, the dosage should not exceed half that of the suggested adult dose. As an adjunct to premedication, the suggested dose is 1.1 mg per kg of body weight in combination with an appropriately reduced dose of narcotic or barbiturate and the appropriate dose of an atropine-like drug (see PRECAUTIONS - Drug Interactions). Antiemetics should not be used in vomiting of unknown etiology in pediatric patients.

Preparation and Administration Instructions for Diluted Intravenous Infusion in Adults

Inspect the solution for particulate matter and discoloration, before dilution, after dilution, and before administration.
Discard the vial, ampule, or bag if particulates and/or discoloration are observed.

1. Determine the recommended dose of promethazine hydrochloride injection.

2. Aseptically withdraw the required volume from the vial or ampule and transfer it into an infusion bag.

- Use a filter needle when withdrawing promethazine hydrochloride injection from the ampule.

3. Dilute with the recommended volume of 0.9% Sodium Chloride Injection, see Table 1. Avoid mixing and/or diluting with any other drugs or solutions other than 0.9% Sodium Chloride Injection.

4. Gently invert the infusion bag.

5. Check patency of the access site before administration.

6. Administer the diluted solution through an intravenous catheter, inserted in a large vein (preferably through a central venous catheter), over 20 to 40 minutes; for maximum infusion rates, see Table 1.

- Do NOT administer via an intravenous catheter in the hand or wrist.

7. If pain occurs at the injection site during intravenous infusion, immediately discontinue the infusion and evaluate for possible arterial injection or perivascular extravasation.

Table 1. Preparation and Infusion Information by Adult Dose of Promethazine Hydrochloride Injection
Dose of Promethazine Hydrochloride Injection | Volume of 0.9% Sodium Chloride Injection for Dilution | Maximum Concentration of the Diluted Promethazine Hydrochloride Injection Solution | Maximum Rate of Infusion
12.5 mg | 50 mL | 1 mg/mL | 2.5 mL/minute
25 mg | 50 mL | 1 mg/mL | 2.5 mL/minute
50 mg | 50 mL | 1 mg/mL | 2.5 mL/minute
75 mg | 100 mL | 1 mg/mL | 5 mL/minute

Preparation and Administration Instructions for Diluted Intravenous Infusion to Pediatric Patients 2 Years of Age and Older

Inspect the solution for particulate matter and discoloration, before dilution, after dilution, and before administration.
Discard the vial, ampule, syringe or bag if particulates and/or discoloration are observed.

1. Determine the recommended dose of promethazine hydrochloride injection for pediatric patients 2 years of age and older.

2. Aseptically withdraw the required volume from the vial or ampule and transfer it into an appropriately sized syringe or bag for use with an infusion pump.

- Use a filter needle when withdrawing promethazine hydrochloride injection from the ampule.

3. Dilute with the recommended volume of 0.9% Sodium Chloride Injection, see Table 2. Avoid mixing and/or diluting with any other drugs or solutions other than 0.9% Sodium Chloride Injection.

4. Gently invert the syringe or bag.

5. Check patency of the access site before administration.

6. Administer the diluted solution through an intravenous catheter, inserted in a large vein (preferably through a central venous catheter) with a maximum infusion rate of 1.25 mL/minute.

- Do NOT administer via an intravenous catheter in the hand or wrist.

7. If pain occurs at the injection site during intravenous infusion, immediately discontinue the infusion and evaluate for possible arterial injection or perivascular extravasation.

Table 2. Preparation and Infusion Information by Pediatric Dose of Promethazine Hydrochloride Injection [Avoid mixing and/or diluting with any other drugs or solutions besides 0.9% Sodium Chloride Injection]
Dose of Promethazine Hydrochloride Injection | Volume of 0.9% Sodium Chloride Injection for Dilution | Maximum Concentration of the Diluted Promethazine Hydrochloride Injection Solution | Maximum Rate of Infusion
Up to 25 mg | 25 mL | 1 mg/mL | 1.25 mL/minute
25 mg to 50 mg | 50 mL | 1 mg/mL | 1.25 mL/minute

Storage of Diluted Promethazine Hydrochloride Injection

Diluted solution may be stored up to 4 hours at room temperature, 20°C to 25°C (68°F to 77°F), or refrigerated at 2°C to 8°C (36° to 46°F), up to 24 hours.

HOW SUPPLIED

Promethazine Hydrochloride Injection, USP is available as follows:

25 mg/mL

Overbagged with 5 x 1 mL vials in each bag, NDC 55154-2861-5

WARNING: This Unit Dose package is not child resistant and is Intended for Institutional Use Only. Keep this and all drugs out of the reach of children.

Storage

Store at 20° to 25°C (68° to 77°F) [See USP Controlled Room Temperature].
Protect from light. Keep covered in carton until time of use.
Do not use if solution has developed color or contains a precipitate.

To report SUSPECTED ADVERSE REACTIONS, contact Hikma Pharmaceuticals USA Inc. at 1-877-845-0689, or the FDA at 1-800-FDA-1088 or www.fda.gov/medwatch.

For Product Inquiry call 1-877-845-0689.

Manufactured by:

Hikma Pharmaceuticals USA Inc.
Berkeley Heights, NJ 07922

Distributed By:

Cardinal Health

Dublin, OH 43017

L35883810126

Revised December 2023

462-232-07

Package/Label Display Panel

NDC 55154-2861-5

PROMETHAZINE HCl INJECTION,

USP 25 mg/mL

5 x 1 mL VIALS